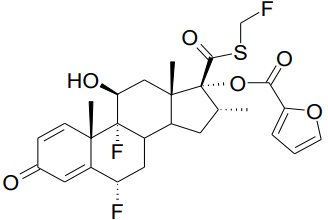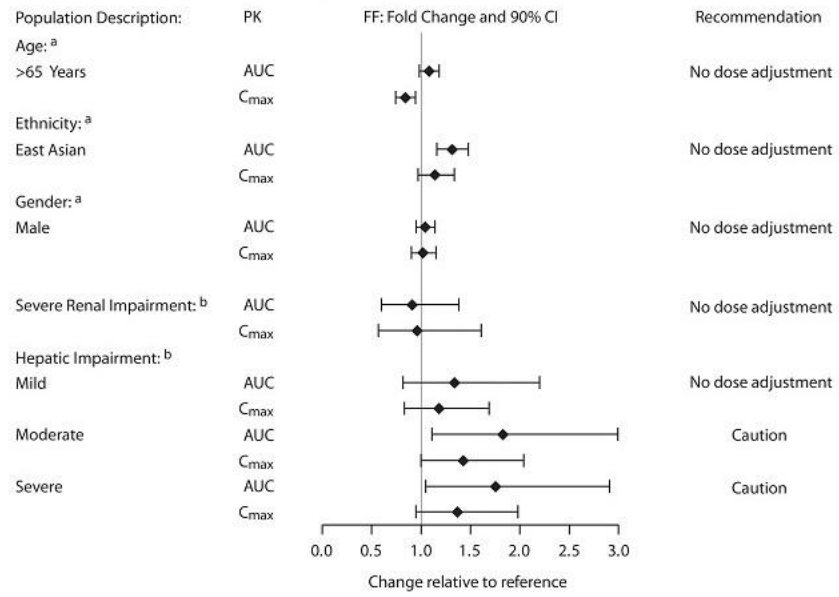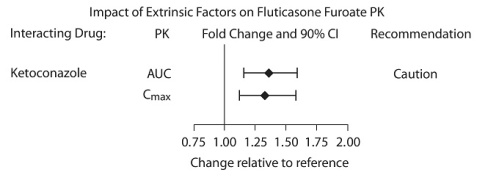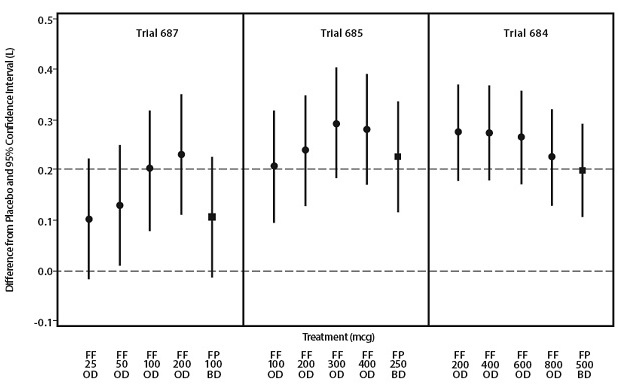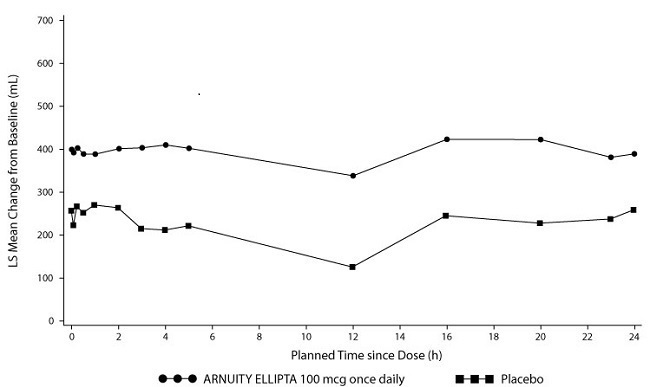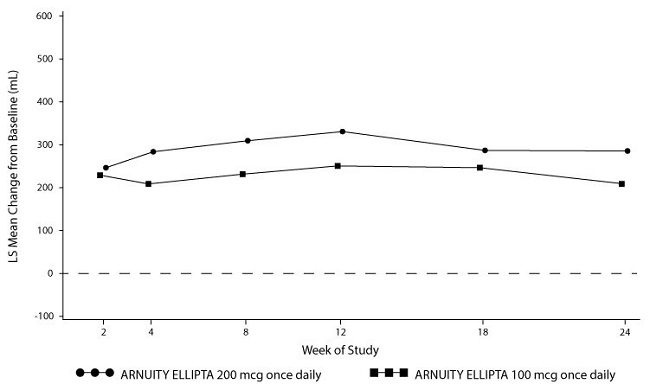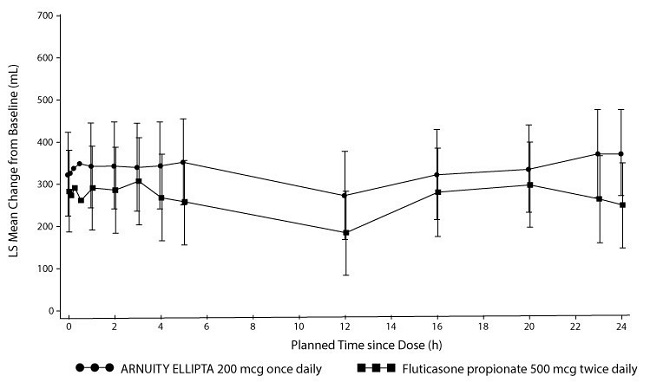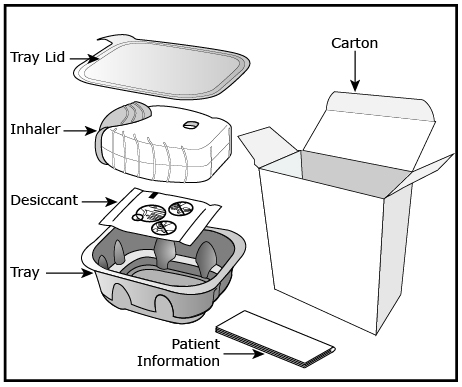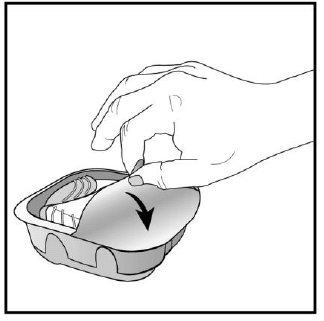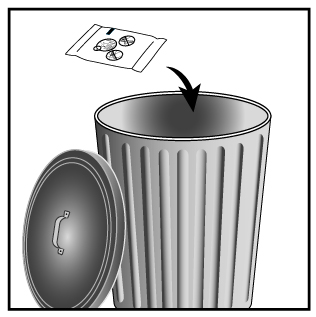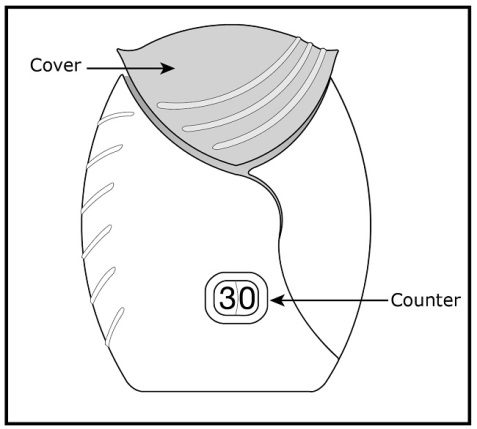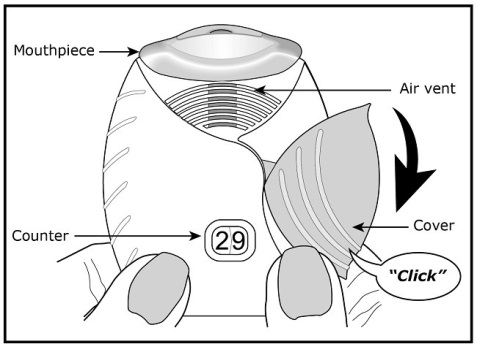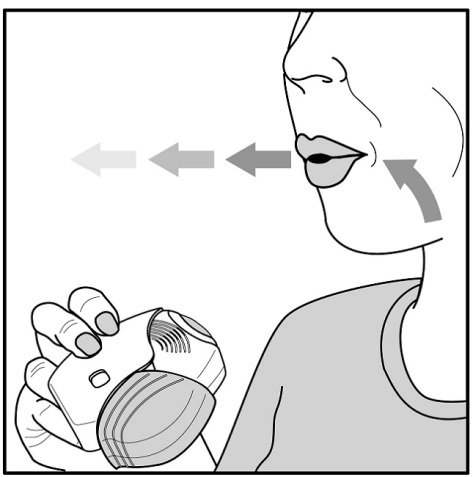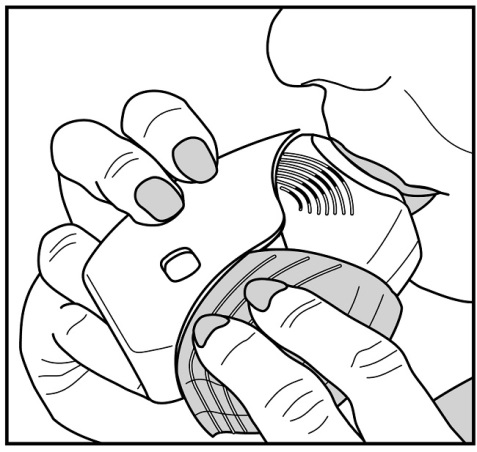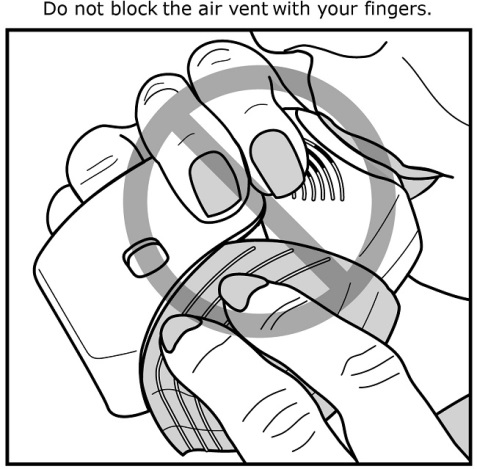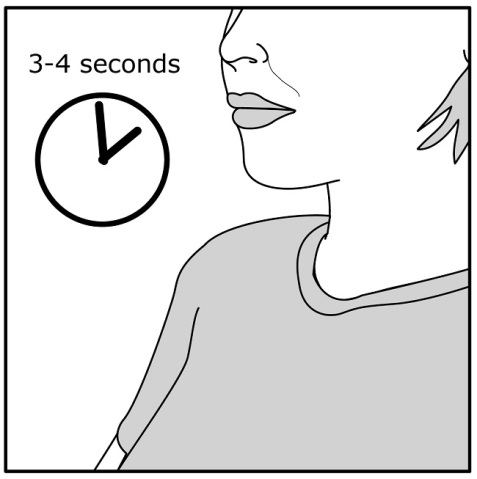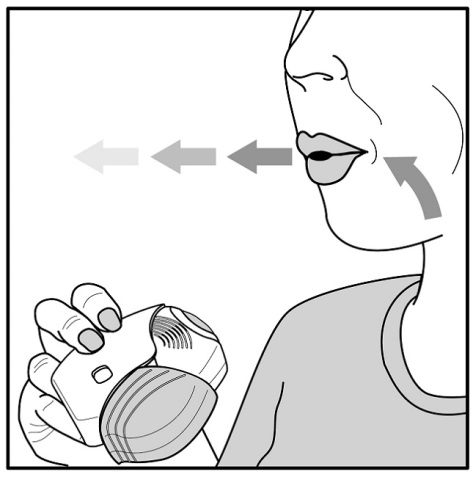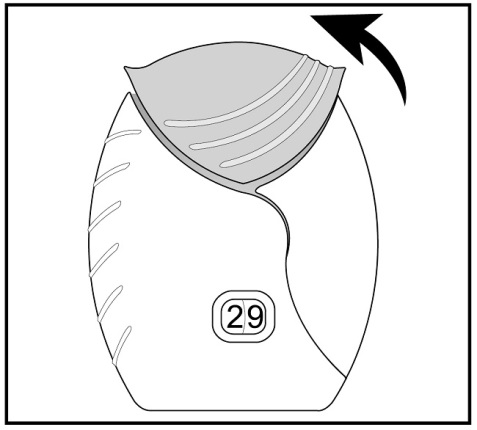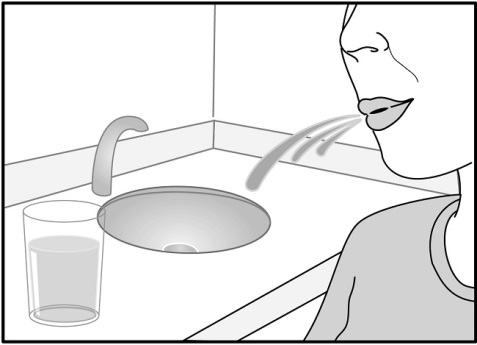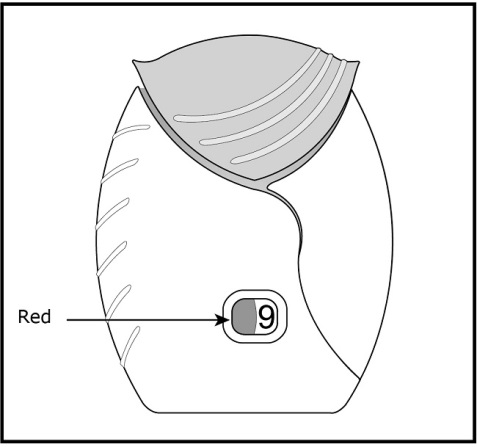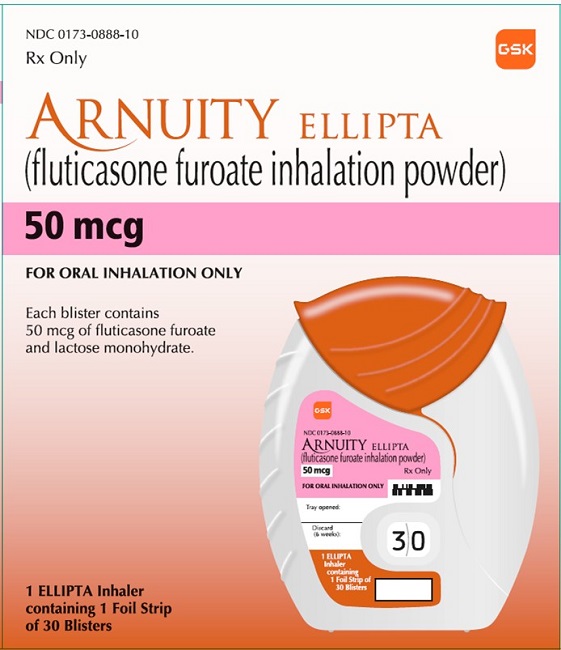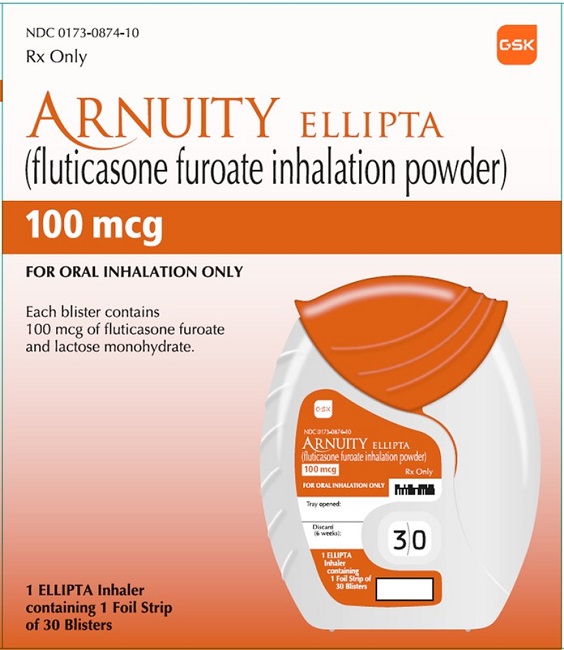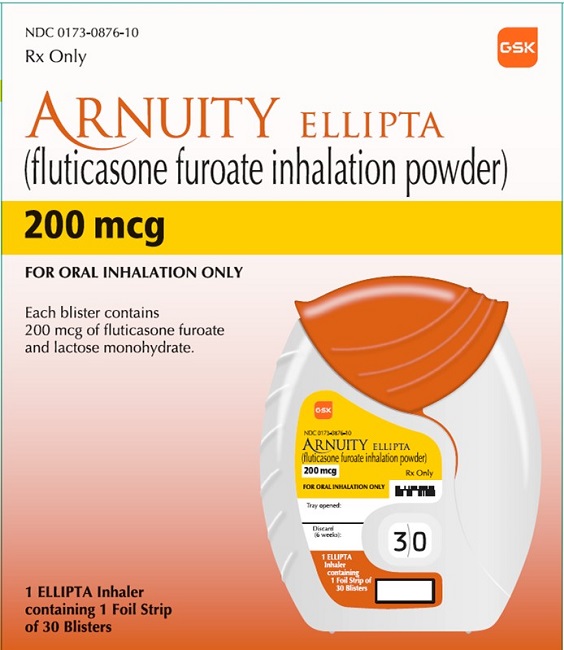 DRUG LABEL: Arnuity Ellipta
NDC: 0173-0888 | Form: POWDER
Manufacturer: GlaxoSmithKline LLC
Category: prescription | Type: HUMAN PRESCRIPTION DRUG LABEL
Date: 20231018

ACTIVE INGREDIENTS: FLUTICASONE FUROATE 50 ug/1 1
INACTIVE INGREDIENTS: LACTOSE MONOHYDRATE

HIGHLIGHTS OF PRESCRIBING INFORMATION

These highlights do not include all the information needed to use ARNUITY ELLIPTA safely and effectively. See full prescribing information for ARNUITY ELLIPTA.
ARNUITY ELLIPTA (fluticasone furoate inhalation powder), for oral inhalation use
Initial U.S. Approval: 2014

1 INDICATIONS AND USAGE

ARNUITY ELLIPTA is an inhaled corticosteroid indicated for the maintenance treatment of asthma in adult and pediatric patients aged 5 years and older. (1)

Limitations of Use: Not indicated for relief of acute bronchospasm. (1, 5.2)

2 DOSAGE AND ADMINISTRATION

- For oral inhalation only. (2.1)
- Maintenance treatment of asthma in adult and pediatric patients aged 12 years and older: The starting dosage, 1 actuation of ARNUITY ELLIPTA 100 mcg or ARNUITY ELLIPTA 200 mcg once daily, is based on prior asthma therapy and disease severity. (2.2)
- Maintenance treatment of asthma in pediatric patients aged 5 to 11 years: 1 actuation of ARNUITY ELLIPTA 50 mcg once daily. (2.2)

3 DOSAGE FORMS AND STRENGTHS

Inhalation powder: A foil blister strip of powder formulation for oral inhalation. Each blister contains 50 mcg, 100 mcg, or 200 mcg of fluticasone furoate. (3)

4 CONTRAINDICATIONS

- Primary treatment of status asthmaticus or acute episodes of asthma requiring intensive measures. (4)
- Severe hypersensitivity to milk proteins (4)
- Demonstrated hypersensitivity to any ingredients. (4)

5 WARNINGS AND PRECAUTIONS

- Candida albicans infection of the mouth and pharynx may occur. Monitor patients periodically. Advise the patient to rinse his/her mouth with water without swallowing after inhalation to help reduce the risk. (5.1)
- Do not use for relief of acute symptoms. Patients require immediate re-evaluation during rapidly deteriorating asthma. (5.2)
- Potential worsening of infections (e.g., existing tuberculosis; fungal, bacterial, viral, or parasitic infections; ocular herpes simplex). Use with caution in patients with these infections. More serious or even fatal course of chickenpox or measles can occur in susceptible patients. (5.3)
- Risk of impaired adrenal function when transferring from systemic corticosteroids. Wean patients slowly from systemic corticosteroids if transferring to ARNUITY ELLIPTA. (5.4)
- Hypercorticism and adrenal suppression may occur with very high dosages or at the regular dosage in susceptible individuals. If such changes occur, discontinue ARNUITY ELLIPTA slowly. (5.5)
- If paradoxical bronchospasm occurs, discontinue ARNUITY ELLIPTA and institute alternative therapy. (5.7)
- Assess for decrease in bone mineral density initially and periodically thereafter. (5.9)
- Monitor growth of pediatric patients. (5.10)
- Glaucoma and cataracts may occur with long-term use of inhaled corticosteroids. Consider referral to an ophthalmologist in patients who develop ocular symptoms or use ARNUITY ELLIPTA long term. (5.11)

6 ADVERSE REACTIONS

Most common adverse reactions reported in ≥5% of adult and pediatric subjects aged 12 years and older are nasopharyngitis, bronchitis, upper respiratory tract infection, and headache. (6.1)

Most common adverse reactions reported in ≥3% of pediatric subjects aged 5 to 11 years are pharyngitis, bronchitis, and viral infection. (6.1)

To report SUSPECTED ADVERSE REACTIONS, contact GlaxoSmithKline at 1-888-825-5249 or FDA at 1-800-FDA-1088 or www.fda.gov/medwatch.

7 DRUG INTERACTIONS

Strong cytochrome P450 3A4 inhibitors (e.g., ketoconazole): Use with caution. May cause systemic corticosteroid effects. (7.1)

8 USE IN SPECIFIC POPULATIONS

Hepatic impairment: Fluticasone furoate systemic exposure may increase in patients with moderate or severe impairment. Monitor for systemic corticosteroid effects. (8.6, 12.3)

FULL PRESCRIBING INFORMATION

1 INDICATIONS AND USAGE

ARNUITY ELLIPTA is indicated for the maintenance treatment of asthma in adult and pediatric patients aged 5 years and older.

Limitations of Use

ARNUITY ELLIPTA is NOT indicated for the relief of acute bronchospasm.

2 DOSAGE AND ADMINISTRATION

2.1 Administration

- Administer 1 actuation of ARNUITY ELLIPTA once daily by oral inhalation.
- After inhalation, the patient should rinse his/her mouth with water without swallowing to help reduce the risk of oropharyngeal candidiasis.
- ARNUITY ELLIPTA should be used at the same time every day. Do not use ARNUITY ELLIPTA more than 1 time every 24 hours.
- The maximum benefit may not be achieved for up to 2 weeks or longer after starting treatment. Individual patients may experience a variable time to onset and degree of symptom relief.

No dosage adjustment is required for geriatric patients, patients with renal impairment, or patients with mild hepatic impairment [see Clinical Pharmacology (12.3)].

2.2 Recommended Dosage

Adult and Pediatric Patients Aged 12 Years and Older

The recommended starting dosage for adult and pediatric patients aged 12 years and older not on an inhaled corticosteroid (ICS) is fluticasone furoate 100 mcg (1 actuation of ARNUITY ELLIPTA 100 mcg) once daily by oral inhalation.

- For other adult and pediatric patients aged 12 years and older, the recommended starting dosage should be based on previous asthma drug therapy and disease severity.
- For adult and pediatric patients aged 12 years and older who do not respond to ARNUITY ELLIPTA 100 mcg after 2 weeks of therapy, replacement with ARNUITY ELLIPTA 200 mcg may provide additional asthma control.
- The maximum recommended dosage in adult and pediatric patients aged 12 years and older is ARNUITY ELLIPTA 200 mcg once daily.
- If asthma symptoms arise in the period between doses, an inhaled, short-acting beta2-agonist (rescue medicine, e.g., albuterol) should be used for immediate relief.
- If a previously effective dosage regimen of ARNUITY ELLIPTA fails to provide adequate improvement in asthma control, the therapeutic regimen should be re-evaluated and additional therapeutic options (e.g., replacing the current strength of ARNUITY ELLIPTA with a higher strength, initiating an ICS and long-acting beta2-agonist [LABA] combination product, initiating oral corticosteroids) should be considered.
- After asthma stability has been achieved, it is desirable to titrate to the lowest effective dosage to help reduce the possibility of adverse reactions.

Pediatric Patients Aged 5 to 11 Years

The recommended dosage for pediatric patients aged 5 to 11 years is fluticasone furoate 50 mcg (1 actuation of ARNUITY ELLIPTA 50 mcg) once daily by oral inhalation [see Warnings and Precautions (5.10)].

3 DOSAGE FORMS AND STRENGTHS

Inhalation powder: Plastic inhaler containing a foil blister strip of powder. Each blister contains fluticasone furoate 50 mcg, 100 mcg, or 200 mcg.

4 CONTRAINDICATIONS

ARNUITY ELLIPTA is contraindicated in the following conditions:

- Primary treatment of status asthmaticus or other acute episodes of asthma where intensive measures are required [see Warnings and Precautions (5.2)].
- Severe hypersensitivity to milk proteins or demonstrated hypersensitivity to fluticasone furoate or any of the excipients [see Warnings and Precautions (5.8), Description (11)].

5 WARNINGS AND PRECAUTIONS

5.1 Oropharyngeal Candidiasis

ARNUITY ELLIPTA contains fluticasone furoate, an ICS. Localized infections of the mouth and pharynx with Candida albicans have occurred in subjects treated with orally inhaled drug products containing fluticasone furoate. When such an infection develops, it should be treated with appropriate local or systemic (i.e., oral) antifungal therapy while treatment with ARNUITY ELLIPTA continues. In some cases, therapy with ARNUITY ELLIPTA may need to be interrupted. Advise the patient to rinse his/her mouth with water without swallowing following administration of ARNUITY ELLIPTA to help reduce the risk of oropharyngeal candidiasis.

5.2 Acute Asthma Episodes

ARNUITY ELLIPTA is not indicated for the relief of acute symptoms, i.e., as rescue therapy for treatment of acute episodes of bronchospasm. ARNUITY ELLIPTA has not been studied in the relief of acute symptoms and extra doses should not be used for that purpose. Acute symptoms should be treated with an inhaled, short-acting beta2-agonist. Instruct patients to contact their healthcare providers immediately if episodes of asthma not responsive to bronchodilators occur during the course of treatment with ARNUITY ELLIPTA. During such episodes, patients may require therapy with oral corticosteroids.

5.3 Immunosuppression and Risk of Infections

Persons who are using drugs that suppress the immune system, such as corticosteroids, including ARNUITY ELLIPTA, are more susceptible to infections than healthy individuals. Chickenpox and measles can have a more serious or even fatal course in susceptible children or adults using corticosteroids. In such children or adults who have not had these diseases or been properly immunized, particular care should be taken to avoid exposure. How the dose, route, and duration of corticosteroid administration affect the risk of developing a disseminated infection is not known. The safety and effectiveness of ARNUITY ELLIPTA have not been established in pediatric patients less than 5 years of age and ARNUITY ELLIPTA is not indicated for use in this population. The contribution of the underlying disease and/or prior corticosteroid treatment to the risk is also not known. If a patient is exposed to chickenpox, prophylaxis with varicella zoster immune globulin (VZIG) or pooled intravenous immunoglobulin (IVIG) may be indicated. If a patient is exposed to measles, prophylaxis with pooled intramuscular immunoglobulin (IG) may be indicated. (See the Prescribing Information for VZIG, IVIG, and IG.) If chickenpox develops, treatment with antiviral agents may be considered.

ICS should be used with caution, if at all, in patients with active or quiescent tuberculosis infections of the respiratory tract; systemic fungal, bacterial, viral, or parasitic infections; or ocular herpes simplex.

5.4 Transferring Patients from Systemic Corticosteroid Therapy

HPA Suppression/Adrenal Insufficiency

Particular care is needed for patients who have been transferred from systemically active corticosteroids to ICS because deaths due to adrenal insufficiency have occurred in patients with asthma during and after transfer from systemic corticosteroids to less systemically available ICS. After withdrawal from systemic corticosteroids, a number of months are required for recovery of hypothalamic-pituitary-adrenal (HPA) function.

Patients who have been previously maintained on 20 mg or more of prednisone (or its equivalent) may be most susceptible, particularly when their systemic corticosteroids have been almost completely withdrawn. During this period of HPA suppression, patients may exhibit signs and symptoms of adrenal insufficiency when exposed to trauma, surgery, or infection (particularly gastroenteritis) or other conditions associated with severe electrolyte loss. Although ARNUITY ELLIPTA may control asthma symptoms during these episodes, in recommended doses it supplies less than normal physiological amounts of glucocorticoid systemically and does NOT provide the mineralocorticoid activity that is necessary for coping with these emergencies.

During periods of stress or a severe asthma attack, patients who have been withdrawn from systemic corticosteroids should be instructed to resume oral corticosteroids (in large doses) immediately and to contact their healthcare practitioner for further instruction. These patients should also be instructed to carry a warning card indicating that they may need supplementary systemic corticosteroids during periods of stress or a severe asthma attack.

Patients requiring oral corticosteroids should be weaned slowly from systemic corticosteroid use after transferring to ARNUITY ELLIPTA. Prednisone reduction can be accomplished by reducing the daily prednisone dose by 2.5 mg on a weekly basis during therapy with ARNUITY ELLIPTA. Lung function (forced expiratory volume in 1 second [FEV1] or peak expiratory flow [PEF]), beta-agonist use, and asthma symptoms should be carefully monitored during withdrawal of oral corticosteroids. In addition, patients should be observed for signs and symptoms of adrenal insufficiency, such as fatigue, lassitude, weakness, nausea and vomiting, and hypotension.

Unmasking of Allergic Conditions Previously Suppressed by Systemic Corticosteroids

Transfer of patients from systemic corticosteroid therapy to ARNUITY ELLIPTA may unmask allergic conditions previously suppressed by the systemic corticosteroid therapy (e.g., rhinitis, conjunctivitis, eczema, arthritis, eosinophilic conditions).

Corticosteroid Withdrawal Symptoms

During withdrawal from oral corticosteroids, some patients may experience symptoms of systemically active corticosteroid withdrawal (e.g., joint and/or muscular pain, lassitude, depression) despite maintenance or even improvement of respiratory function.

5.5 Hypercorticism and Adrenal Suppression

ARNUITY ELLIPTA will often help control asthma symptoms with less suppression of HPA function than therapeutically equivalent oral doses of prednisone. Since ARNUITY ELLIPTA is absorbed into the circulation and can be systemically active at higher doses, the beneficial effects of ARNUITY ELLIPTA in minimizing HPA dysfunction may be expected only when recommended dosages are not exceeded and individual patients are titrated to the lowest effective dose.

Because of the possibility of significant systemic absorption of ICS in sensitive patients, patients treated with ARNUITY ELLIPTA should be observed carefully for any evidence of systemic corticosteroid effects. Particular care should be taken in observing patients postoperatively or during periods of stress for evidence of inadequate adrenal response.

It is possible that systemic corticosteroid effects such as hypercorticism and adrenal suppression (including adrenal crisis) may appear in a small number of patients, particularly when fluticasone furoate is administered at higher than recommended doses over prolonged periods of time. If such effects occur, reduce the dose of ARNUITY ELLIPTA slowly, consistent with accepted procedures for reducing systemic corticosteroids, and consider other treatments for management of asthma symptoms.

5.6 Drug Interactions with Strong Cytochrome P450 3A4 Inhibitors

Caution should be exercised when considering the coadministration of ARNUITY ELLIPTA with ketoconazole and other known strong CYP3A4 inhibitors (including, but not limited to, ritonavir, clarithromycin, conivaptan, indinavir, itraconazole, lopinavir, nefazodone, nelfinavir, saquinavir, telithromycin, troleandomycin, voriconazole) because increased systemic corticosteroid adverse effects may occur [see Drug Interactions (7.1), Clinical Pharmacology (12.3)].

5.7 Paradoxical Bronchospasm

As with other inhaled therapies, ARNUITY ELLIPTA can produce paradoxical bronchospasm, which may be life threatening. If paradoxical bronchospasm occurs following dosing with ARNUITY ELLIPTA, it should be treated immediately with an inhaled, short-acting bronchodilator; ARNUITY ELLIPTA should be discontinued immediately; and alternative therapy should be instituted.

5.8 Hypersensitivity Reactions, Including Anaphylaxis

Hypersensitivity reactions such as anaphylaxis, angioedema, urticaria, flushing, allergic dermatitis, and bronchospasm may occur after administration of ARNUITY ELLIPTA. Discontinue ARNUITY ELLIPTA if such reactions occur. There have been reports of anaphylactic reactions in patients with severe milk protein allergy after inhalation of other powder medications containing lactose; therefore, patients with severe milk protein allergy should not use ARNUITY ELLIPTA [see Contraindications (4)].

5.9 Reduction in Bone Mineral Density

Decreases in bone mineral density (BMD) have been observed with long-term administration of products containing ICS. The clinical significance of small changes in BMD with regard to long-term consequences such as fracture is unknown. Patients with major risk factors for decreased bone mineral content, such as prolonged immobilization, family history of osteoporosis, postmenopausal status, tobacco use, advanced age, poor nutrition, or chronic use of drugs that can reduce bone mass (e.g., anticonvulsants, oral corticosteroids) should be monitored and treated with established standards of care.

5.10 Effect on Growth

Orally inhaled corticosteroids, including ARNUITY ELLIPTA, may cause a reduction in growth velocity when administered to pediatric patients. The safety and effectiveness of ARNUITY ELLIPTA have not been established in pediatric patients less than 5 years of age. Monitor the growth of pediatric patients receiving ARNUITY ELLIPTA routinely (e.g., via stadiometry). To minimize the systemic effects of orally inhaled corticosteroids, including ARNUITY ELLIPTA, titrate each patient’s dose to the lowest dosage that effectively controls his/her symptoms [see Dosage and Administration (2.2), Use in Specific Populations (8.4)].

5.11 Glaucoma and Cataracts

Glaucoma, increased intraocular pressure, and cataracts have been reported in patients with asthma following the long-term administration of ICS, including fluticasone furoate. Consider referral to an ophthalmologist in patients who develop ocular symptoms or use ARNUITY ELLIPTA long term.

6 ADVERSE REACTIONS

Systemic and local corticosteroid use may result in the following:

- Oropharyngeal Candidiasis [see Warnings and Precautions (5.1)]
- Immunosuppression and Risk of Infections [see Warnings and Precautions (5.3)]
- Hypercorticism and Adrenal Suppression [see Warnings and Precautions (5.5)]
- Reduction in BMD [see Warnings and Precautions (5.9)]
- Growth Effects in Pediatrics [see Warnings and Precautions (5.10)]
- Glaucoma and Cataracts [see Warnings and Precautions (5.11)]

6.1 Clinical Trials Experience

Because clinical trials are conducted under widely varying conditions, adverse reaction rates observed in the clinical trials of a drug cannot be directly compared with rates in the clinical trials of another drug and may not reflect the rates observed in practice.

Adult and Pediatric Subjects Aged 12 Years and Older

The safety of ARNUITY ELLIPTA was evaluated in 10 double-blind, parallel-group, controlled trials (7 with placebo) of 8 to 76 weeks’ duration that enrolled 6,219 subjects with asthma. Doses of fluticasone furoate studied ranged from 25 to 800 mcg.

ARNUITY ELLIPTA 100 mcg was studied in 1,663 subjects, and ARNUITY ELLIPTA 200 mcg was studied in 608 subjects. Subject ages ranged from 12 to 84 years, 65% were female, and 75% were Caucasian.

In these trials, the proportion of subjects who discontinued study treatment early due to adverse reactions was 2% for subjects treated with both ARNUITY ELLIPTA 100 mcg and ARNUITY ELLIPTA 200 mcg and ≤1% for placebo-treated subjects. Serious adverse events, whether considered drug-related or not by the investigators, that occurred in more than 1 subject and in a greater percentage of subjects treated with ARNUITY ELLIPTA than placebo included hypertension, abscess, breast cancer, traumatic limb amputation, subarachnoid hemorrhage, and intervertebral disc protrusion; all events occurred at rates ≤1%.

The incidence of adverse reactions associated with ARNUITY ELLIPTA 100 mcg is shown in Table 1 and is based on one 24-week trial (Trial 1) in adult and pediatric subjects aged 12 years and older with asthma.

Table 1. Adverse Reactions with ARNUITY ELLIPTA 100 mcg with ≥3% Incidence and More Common than Placebo (Trial 1, Intent-to-Treat Population)
Adverse Reaction | ARNUITY ELLIPTA 100 mcg; (n = 114); % | Placebo; (n = 115); %
Nasopharyngitis | 8 | 5
Bronchitis | 7 | 6
Upper respiratory tract infection | 6 | 5
Headache | 6 | 4
Pharyngitis | 4 | 3
Sinusitis | 4 | <1
Toothache | 3 | <1
Gastroenteritis viral | 3 | 0
Oral candidiasis | 3 | 0
Oropharyngeal candidiasis | 3 | 0
Oropharyngeal pain | 3 | 0

The incidence of adverse reactions associated with ARNUITY ELLIPTA 200 mcg is shown in Table 2 and is based on one 24-week trial (Trial 3) in adult and pediatric subjects aged 12 years and older with asthma. This trial did not have a placebo arm.

Table 2. Adverse Reactions with ARNUITY ELLIPTA 200 mcg with ≥3% Incidence (Trial 3, Safety Population)
Adverse Reaction | ARNUITY ELLIPTA; 200 mcg; (n = 119); % | ARNUITY ELLIPTA; 100 mcg; (n = 119); %
Nasopharyngitis | 13 | 12
Headache | 13 | 10
Bronchitis | 7 | 12
Influenza | 7 | 4
Upper respiratory tract infection | 6 | 2
Sinusitis | 4 | 7
Oropharyngeal pain | 4 | 3
Pharyngitis | 3 | 6
Back pain | 3 | 3
Dysphonia | 3 | 2
Oral candidiasis | 3 | <1
Procedural pain | 3 | <1
Rhinitis | 3 | <1
Throat irritation | 3 | <1
Abdominal pain | 3 | 0
Cough | 3 | 0

Adverse reactions observed in the other trials were consistent with those described in Tables 1 and 2.

Long-term Safety

Long-term safety data are based on 2 trials in adult and pediatric subjects aged 12 years and older with asthma. In one 52-week trial, subjects received fluticasone furoate 100 mcg (n = 201) or fluticasone furoate 200 mcg (n = 202) in combination with a LABA. Subjects had a mean age of 39 years (pediatric patients 12 years and older made up 16% of the population), 63% were female, and 67% were Caucasian. In addition to the events shown in Table 1 and Table 2, adverse events occurring in ≥3% of the subjects treated with fluticasone furoate 100 mcg or fluticasone furoate 200 mcg, in combination with a LABA, included pyrexia, extrasystoles, upper abdominal pain, respiratory tract infection, diarrhea, and allergic rhinitis.

In a second 24- to 76-week trial, subjects received fluticasone furoate 100 mcg (n = 1,010). Subjects participating in this trial had a history of 1 or more asthma exacerbations that required treatment with oral/systemic corticosteroids or emergency department visit or in-patient hospitalization for the treatment of asthma within the previous 12 months. Subjects had a mean age of 42 years (pediatric patients 12 years and older made up 14% of the population), 67% were female, and 73% were Caucasian. In addition to the events shown in Table 1 and Table 2, adverse events occurring in ≥3% of subjects treated with fluticasone furoate 100 mcg for up to 76 weeks included allergic rhinitis, nasal congestion, and arthralgia.

Pediatric Subjects Aged 5 to 11 Years

The safety data for pediatric subjects is based upon one 12-week clinical trial that enrolled 593 subjects with asthma aged 5 to 11 years. Dosages of fluticasone furoate studied were 25, 50, or 100 mcg administered once daily. ARNUITY ELLIPTA 50 mcg was studied in 120 subjects (46 females and 74 males) [see Clinical Studies (14.2)]. Adverse reactions (≥3% and greater than placebo) seen in pediatric subjects were similar to those reported in adult and pediatric subjects aged 12 years and older. Adverse reactions occurring in ≥3% of subjects treated with ARNUITY ELLIPTA 50 mcg and greater than placebo were pharyngitis, bronchitis, and viral infection.

6.2 Postmarketing Experience

In addition to adverse reactions reported from clinical trials, the following adverse reactions have been identified during postapproval use of ARNUITY ELLIPTA. Because these reactions are reported voluntarily from a population of uncertain size, it is not always possible to reliably estimate their frequency or establish a causal relationship to drug exposure. These events have been chosen for inclusion due to either their seriousness, frequency of reporting, or causal connection to ARNUITY ELLIPTA or a combination of these factors.

Immune System Disorders

Hypersensitivity reactions including anaphylaxis, angioedema, rash, and urticaria.

7 DRUG INTERACTIONS

7.1 Inhibitors of Cytochrome P450 3A4

Fluticasone furoate is a substrate of CYP3A4. Concomitant administration of the strong CYP3A4 inhibitor ketoconazole increases the systemic exposure to fluticasone furoate. Caution should be exercised when considering the coadministration of ARNUITY ELLIPTA with ketoconazole and other known strong CYP3A4 inhibitors [see Warnings and Precautions (5.6), Clinical Pharmacology (12.3)].

8 USE IN SPECIFIC POPULATIONS

8.1 Pregnancy

Risk Summary

There are insufficient data on the use of ARNUITY ELLIPTA in pregnant women to inform a drug-associated risk (see Clinical Considerations). In animal reproduction studies, fluticasone furoate administered by inhalation to rats and rabbits during the period of organogenesis produced no fetal structural abnormalities. The highest fluticasone furoate doses in the rat and rabbit studies were 4 times and 1 time, respectively, the maximum recommended human daily inhalation dose (MRHDID) (see Data.).

The estimated risk of major birth defects and miscarriage for the indicated populations is unknown. In the U.S. general population, the estimated risk of major birth defects and miscarriage in clinically recognized pregnancies is 2% to 4% and 15% to 20%, respectively.

Clinical Considerations

Disease-Associated Maternal and/or Embryofetal Risk: In women with poorly or moderately controlled asthma, there is an increased risk of several perinatal outcomes such as pre-eclampsia in the mother and prematurity, low birth weight, and small for gestational age in the neonate.

Pregnant women should be closely monitored and medication adjusted as necessary to maintain optimal control of asthma.

Data

Animal Data: Fluticasone Furoate: In 2 separate embryofetal developmental studies, pregnant rats and rabbits received fluticasone furoate during the period of organogenesis at doses up to approximately 4 and 1 times, respectively, the MRHDID (on a mcg/m^2 basis at maternal inhalation doses up to 91 and 8 mcg/kg/day, respectively). No evidence of structural abnormalities in fetuses was observed in either species. In a perinatal and postnatal developmental study in rats, dams received fluticasone furoate during late gestation and lactation periods at doses up to approximately 1 time the MRHDID (on a mcg/m^2 basis at maternal inhalation doses up to 27 mcg/kg/day). No evidence of effects on offspring development was observed.

8.2 Lactation

Risk Summary

There is no information available on the presence of fluticasone furoate in human milk, the effects on the breastfed child, or the effects on milk production. Low concentrations of other ICS have been detected in human milk. The developmental and health benefits of breastfeeding should be considered along with the mother’s clinical need for ARNUITY ELLIPTA and any potential adverse effects on the breastfed child from fluticasone furoate or from the underlying maternal condition.

8.4 Pediatric Use

The safety and effectiveness of ARNUITY ELLIPTA for maintenance treatment of asthma have been established in pediatric patients aged 5 years and older. Use of ARNUITY ELLIPTA for this indication in patients 12 years of age and older is supported by evidence from 4 adequate and well-controlled trials in adult and pediatric patients 12 years of age and older. Use of ARNUITY ELLIPTA for this indication in patients 5 to 11 years of age is supported by evidence from an adequate and well-controlled trial in patients 5 to 11 years of age [see Dosage and Administration (2.2), Adverse Reactions (6.1), and Clinical Studies (14.2)].

The safety and effectiveness of ARNUITY ELLIPTA have not been established in pediatric patients less than 5 years of age.

Effects on Growth

Orally inhaled corticosteroids may cause a reduction in growth velocity when administered to pediatric patients. A reduction of growth velocity in these patients may occur as a result of poorly controlled asthma or from use of corticosteroids, including ICS. The effects of long-term treatment of pediatric patients with ICS, including fluticasone furoate, on final adult height are not known.

Controlled clinical trials have shown that ICS may cause a reduction in growth in children. In these trials, the mean reduction in growth velocity was approximately 1 cm/year (range: 0.3 to 1.8 cm/year) and appears to be related to dose and duration of exposure. This effect has been observed in the absence of laboratory evidence of HPA axis suppression, suggesting that growth velocity is a more sensitive indicator of systemic corticosteroid exposure in children than some commonly used tests of HPA axis function. The long-term effects of this reduction in growth velocity associated with orally inhaled corticosteroids, including the impact on final adult height, are unknown. The potential for “catch-up” growth following discontinuation of treatment with orally inhaled corticosteroids has not been adequately studied. The growth of pediatric patients receiving orally inhaled corticosteroids, including ARNUITY ELLIPTA, should be monitored routinely (e.g., via stadiometry). The potential growth effects of prolonged treatment should be weighed against the clinical benefits obtained and the risks associated with alternative therapies. To minimize the systemic effects of orally inhaled corticosteroids, including ARNUITY ELLIPTA, each patient should be titrated to the lowest dose that effectively controls his/her symptoms.

A randomized, double-blind, parallel-group, multicenter, 1-year, placebo-controlled trial evaluated the effect of once-daily treatment with ARNUITY ELLIPTA 50 mcg on growth velocity assessed by stadiometry. The subjects were 457 prepubertal children (girls aged 5 to younger than 8 years and boys aged 5 to younger than 9 years). Mean growth velocity over the 52-week treatment period was lower in the subjects receiving ARNUITY ELLIPTA (5.90 cm/year) compared with placebo (6.06 cm/year). The mean difference in growth velocity was -0.16 cm/year (95% CI: -0.46, 0.14) [see Warnings and Precautions (5.10)].

8.5 Geriatric Use

For the 4 confirmatory trials, 71 subjects were aged 65 years and older (56 of which were treated with ARNUITY ELLIPTA) and 5 were aged 75 years and older (1 of which was treated with ARNUITY ELLIPTA) [see Clinical Studies (14.2)]. Based on available data, no adjustment of the dosage of ARNUITY ELLIPTA in geriatric patients is necessary, but greater sensitivity in some older individuals cannot be ruled out. Clinical trials of ARNUITY ELLIPTA did not include sufficient numbers of subjects aged 65 years and older to determine whether they respond differently from younger subjects. Other reported clinical experience has not identified differences in responses between the elderly and younger subjects. In general, dose selection for an elderly patient should be cautious, usually starting at the low end of the dosing range, reflecting the greater frequency of decreased hepatic, renal, or cardiac function and of concomitant disease or other drug therapy.

8.6 Hepatic Impairment

Fluticasone furoate systemic exposure increased by up to 3-fold in adult subjects with hepatic impairment compared with healthy subjects. Use ARNUITY ELLIPTA with caution in patients with moderate or severe hepatic impairment. Monitor patients for corticosteroid-related side effects. The effect of hepatic impairment on fluticasone furoate systemic exposure in subjects aged younger than 18 years has not been evaluated [see Clinical Pharmacology (12.3)].

8.7 Renal Impairment

There were no significant increases in fluticasone furoate exposure in subjects with severe renal impairment (CrCl <30 mL/min) compared with healthy subjects. No dosage adjustment is required in patients with renal impairment [see Clinical Pharmacology (12.3)].

10 OVERDOSAGE

No human overdosage data have been reported for ARNUITY ELLIPTA. The potential for acute toxic corticosteroid effects following overdosage with ARNUITY ELLIPTA is low. Because of low systemic bioavailability (13.9%) and an absence of acute drug-related systemic findings in clinical trials, overdosage of fluticasone furoate is unlikely to require any treatment other than observation. If used at excessive doses for prolonged periods, systemic effects such as hypercorticism may occur [see Warnings and Precautions (5.5)].

Single- and repeat-dose trials of fluticasone furoate at doses of 50 to 4,000 mcg have been studied in human subjects. Decreases in mean serum cortisol were observed at dosages of 500 mcg or higher given once daily for 14 days.

11 DESCRIPTION

ARNUITY ELLIPTA is an inhalation powder drug product for delivery of fluticasone furoate (an ICS) to patients by oral inhalation.

Fluticasone furoate, a synthetic trifluorinated corticosteroid, has the chemical name (6α,11β,16α,17α)-6,9-difluoro-17-{[(fluoro-methyl)thio]carbonyl}-11-hydroxy-16-methyl-3-oxoandrosta-1,4-dien-17-yl 2-furancarboxylate and the following chemical structure:

Fluticasone furoate is a white powder with a molecular weight of 538.6, and the empirical formula is C27H29F3O6S. It is practically insoluble in water.

ARNUITY ELLIPTA is a light grey and orange plastic inhaler containing a foil blister strip. Each blister on the strip contains a white powder blend of micronized fluticasone furoate (50, 100, or 200 mcg) and lactose monohydrate (12.45, 12.40, or 12.30 mg, respectively) for a total powder blend of 12.5 mg per blister. The lactose monohydrate contains milk proteins. After the inhaler is activated, the powder within the blister is exposed and ready for dispersion into the airstream created by the patient inhaling through the mouthpiece.

Under standardized in vitro test conditions, ARNUITY ELLIPTA 50 mcg, ARNUITY ELLIPTA 100 mcg, and ARNUITY ELLIPTA 200 mcg delivers 46, 90, and 182 mcg, respectively, of fluticasone furoate per dose when tested at a flow rate of 60 L/min for 4 seconds.

In adult subjects with asthma and a mean FEV1 of 2.55 L/sec (range: 1.63 to 3.97 L/sec), mean peak inspiratory flow through the ELLIPTA inhaler was 103.2 L/min (range: 71.2 to 133.1 L/min). In pediatric subjects with asthma aged 5 to 11 years and a mean peak expiratory flow rate of 242 L/min (range: 130 to 420 L/min), mean peak inspiratory flow through the ELLIPTA inhaler was 51.8 L/min (range: 26.8 to 89.9 L/min). Therefore, the ELLIPTA inhaler is able to deliver the dose of fluticasone furoate in patients with asthma.

The actual amount of drug delivered to the lung will depend on patient factors, such as inspiratory flow profile.

12 CLINICAL PHARMACOLOGY

12.1 Mechanism of Action

Fluticasone furoate is a synthetic trifluorinated corticosteroid with anti‑inflammatory activity. Fluticasone furoate has been shown in vitro to exhibit a binding affinity for the human glucocorticoid receptor that is approximately 29.9 times that of dexamethasone and 1.7 times that of fluticasone propionate. The clinical relevance of these findings is unknown.

The precise mechanism through which fluticasone furoate affects asthma symptoms is not known. Inflammation is an important component in the pathogenesis of asthma. Corticosteroids have been shown to have a wide range of actions on multiple cell types (e.g., mast cells, eosinophils, neutrophils, macrophages, lymphocytes) and mediators (e.g., histamine, eicosanoids, leukotrienes, cytokines) involved in inflammation. Specific effects of fluticasone furoate demonstrated in in vitro and in vivo models included activation of the glucocorticoid response element, inhibition of pro-inflammatory transcription factors such as NFkB, and inhibition of antigen-induced lung eosinophilia in sensitized rats. These anti-inflammatory actions of corticosteroids may contribute to their efficacy.

Though effective for the treatment of asthma, corticosteroids may not affect symptoms immediately. Individual patients will experience a variable time to onset and degree of symptom relief. Maximum benefit may not be achieved for 1 to 2 weeks or longer after starting treatment. When corticosteroids are discontinued, asthma stability may persist for several days or longer.

Trials in subjects with asthma have shown a favorable ratio between topical anti-inflammatory activity and systemic corticosteroid effects with recommended doses of orally inhaled fluticasone furoate. This is explained by a combination of a relatively high local anti-inflammatory effect, negligible oral systemic bioavailability (approximately 1.3%), and the minimal pharmacological activity of the metabolites detected in man.

12.2 Pharmacodynamics

The pharmacodynamics of fluticasone furoate was characterized in trials of fluticasone furoate given as a single component and also in trials of fluticasone furoate given in combination with vilanterol.

Cardiac Electrophysiology

A QT/QTc trial did not demonstrate an effect of fluticasone furoate administration on the QTc interval. The effect of a single dose of 4,000 mcg of orally inhaled fluticasone furoate on the QTc interval was evaluated over 24 hours in 40 healthy male and female subjects in a placebo- and positive-controlled (a single dose of 400 mg oral moxifloxacin) cross-over trial. The QTcF maximal mean change from baseline following fluticasone furoate was similar to that observed with placebo with a treatment difference of 0.788 msec (90% CI: -1.802, 3.378). In contrast, moxifloxacin given as a 400-mg tablet resulted in prolongation of the QTcF maximal mean change from baseline compared with placebo with a treatment difference of 9.929 msec (90% CI: 7.339, 12.520).

Hypothalamic-Pituitary-Adrenal Axis Effects

Healthy Subjects: Inhaled fluticasone furoate at repeat doses up to 400 mcg was not associated with statistically significant decreases in serum or urinary cortisol in healthy subjects. Decreases in serum and urine cortisol levels were observed at fluticasone furoate exposures several-fold higher than exposures observed at the therapeutic dose.

Subjects with Asthma: A randomized, double-blind, parallel-group trial in 104 pediatric subjects with asthma (aged 5 to 11 years) showed no difference between once-daily treatment with ARNUITY ELLIPTA 50 mcg compared with placebo on serum cortisol weighted mean (0 to 24 hours) and serum cortisol AUC(0-24) following 6 weeks of treatment.

A randomized, double-blind, parallel-group trial in 185 subjects with asthma aged 12 to 65 years showed no difference between once-daily treatment with fluticasone furoate/vilanterol 100/25 mcg or fluticasone furoate/vilanterol 200/25 mcg compared with placebo on serum cortisol weighted mean (0 to 24 hours), serum cortisol AUC(0-24), and 24-hour urinary cortisol after 6 weeks of treatment, whereas prednisolone 10 mg given once daily for 7 days resulted in significant cortisol suppression.

12.3 Pharmacokinetics

The pharmacokinetics of fluticasone furoate was characterized in trials of fluticasone furoate given as a single component and in trials of fluticasone furoate given in combination with vilanterol. Linear pharmacokinetics was observed for fluticasone furoate (200 to 800 mcg). On repeated once-daily inhalation administration, steady state of fluticasone furoate plasma concentration was achieved after 6 days, and the accumulation was up to 2.6-fold as compared with single dose.

Absorption

Fluticasone furoate plasma levels may not predict therapeutic effect. Peak plasma concentrations are reached within 0.5 to 1 hour. Absolute bioavailability of fluticasone furoate when administrated by inhalation was 13.9%, primarily due to absorption of the inhaled portion of the dose delivered to the lung. Oral bioavailability from the swallowed portion of the dose is low (approximately 1.3%) due to extensive first-pass metabolism. Systemic exposure (AUC) in subjects with asthma was 26% lower than observed in healthy subjects.

Distribution

Following intravenous administration to healthy subjects, the mean volume of distribution at steady state was 661 L. Binding of fluticasone furoate to human plasma proteins was high (99.6%).

Elimination

Metabolism: Fluticasone furoate is cleared from systemic circulation principally by hepatic metabolism via CYP3A4 to metabolites with significantly reduced corticosteroid activity. There was no in vivo evidence for cleavage of the furoate moiety resulting in the formation of fluticasone.

Excretion: Fluticasone furoate and its metabolites are eliminated primarily in the feces, accounting for approximately 101% and 90% of the orally and intravenously administered doses, respectively. Urinary excretion accounted for approximately 1% and 2% of the orally and intravenously administered doses, respectively. Following repeat-dose inhaled administration, the plasma elimination phase half-life averaged 24 hours.

Specific Populations

The effects of renal and hepatic impairment and other intrinsic factors on the pharmacokinetics of fluticasone furoate are shown in Figure 1.

Figure 1. Impact of Intrinsic Factors on the Pharmacokinetics (PK) of Fluticasone Furoate (FF)

a Age, gender, and ethnicity comparison for ARNUITY ELLIPTA in adult and pediatric subjects aged 12 years and older with asthma.
b Renal groups (fluticasone furoate/vilanterol 200 mcg/25 mcg) and hepatic groups (fluticasone furoate/vilanterol 200 mcg/25 mcg or fluticasone furoate/vilanterol 100 mcg/12.5 mcg) compared with healthy control group.

Pediatric Patients: A population pharmacokinetics analysis to assess impact of age on fluticasone furoate systemic exposure was conducted using combined data from clinical trials in pediatric subjects aged 5 to 11 years (n = 306). There was no relevant effect of age on the apparent clearance of fluticasone furoate. The rate and extent of fluticasone furoate systemic exposure at steady state in children aged 5 to 11 years were comparable to that observed in adult and pediatric subjects aged 12 years and older following dosing with fluticasone furoate 100 mcg monotherapy.

Racial or Ethnic Groups: Systemic exposure [AUC(0-24)] to inhaled fluticasone furoate 200 mcg was 27% to 49% higher in healthy subjects of Japanese, Korean, and Chinese heritage compared with White subjects. Similar differences were observed for subjects with asthma (Figure 1). However, there is no evidence that this higher exposure to fluticasone furoate results in clinically relevant effects on urinary cortisol excretion or on efficacy in these racial groups.

Patients with Hepatic Impairment: Following repeat dosing of fluticasone furoate/vilanterol 200/25 mcg (100/12.5 mcg in the severe impairment group) for 7 days, there was an increase of 34%, 83%, and 75% in fluticasone furoate systemic exposure (AUC) in subjects with mild, moderate, and severe hepatic impairment, respectively, compared with healthy subjects (Figure 1).

In subjects with moderate hepatic impairment receiving fluticasone furoate/vilanterol 200/25 mcg, mean serum cortisol (0 to 24 hours) was reduced by 34% (90% CI: 11%, 51%) compared with healthy subjects. In subjects with severe hepatic impairment receiving fluticasone furoate/vilanterol 100/12.5 mcg, mean serum cortisol (0 to 24 hours) was increased by 14% (90% CI: -16%, 55%) compared with healthy subjects. Patients with moderate to severe hepatic disease should be closely monitored.

Patients with Renal Impairment: Fluticasone furoate systemic exposure was not increased in subjects with severe renal impairment compared with healthy subjects (Figure 1). There was no evidence of greater corticosteroid class-related systemic effects (assessed by serum cortisol) in subjects with severe renal impairment compared with healthy subjects.

Drug Interaction Studies

The potential for fluticasone furoate to inhibit or induce metabolic enzymes and transporter systems is negligible at low inhalation doses.

Inhibitors of Cytochrome P450 3A4: The exposure (AUC) of fluticasone furoate was 36% higher after single and repeated doses when coadministered with ketoconazole 400 mg compared with placebo (Figure 2). The increase in fluticasone furoate exposure was associated with a 27% reduction in weighted mean serum cortisol (0 to 24 hours).

Figure 2. Impact of Coadministered Ketoconazolea on the Pharmacokinetics (PK) of Fluticasone Furoate

a Compared with placebo group.

13 NONCLINICAL TOXICOLOGY

13.1 Carcinogenesis, Mutagenesis, Impairment of Fertility

Fluticasone furoate produced no treatment-related increases in the incidence of tumors in 2-year inhalation studies in rats and mice at inhaled doses up to 9 and 19 mcg/kg/day, respectively (less than the MRHDID on a mcg/m^2 basis).

Fluticasone furoate did not induce gene mutation in bacteria or chromosomal damage in a mammalian cell mutation test in mouse lymphoma L5178Y cells in vitro. There was also no evidence of genotoxicity in the in vivo micronucleus test in rats.

No evidence of impairment of fertility was observed in male and female rats at inhaled fluticasone furoate doses up to 29 and 91 mcg/kg/day, respectively (approximately 1 and 4 times, respectively, the MRHDID for adults on a mcg/m^2 basis).

14 CLINICAL STUDIES

The safety and efficacy of ARNUITY ELLIPTA were evaluated in 3,611 adult and pediatric subjects aged 12 years and older with asthma. The development program included 4 confirmatory trials of 3 and 6 months’ duration and 3 dose-ranging trials of 8 weeks’ duration. The efficacy of ARNUITY ELLIPTA is based primarily on the dose-ranging trials and the confirmatory trials described below. One additional trial evaluated the safety and efficacy of ARNUITY ELLIPTA in 593 subjects aged 5 to 11 years.

14.1 Dose-Ranging Trials

Eight doses of fluticasone furoate ranging from 25 to 800 mcg once daily were evaluated in 3 randomized, double-blind, placebo-controlled, 8-week trials in adult and pediatric subjects aged 12 years and older with asthma. Across the 3 trials, subjects were uncontrolled at baseline on treatments of short-acting beta2-agonist and/or non-corticosteroid controller medications (Trial 687 NCT00603382), low-dose ICS (Trial 685 NCT00603278), or medium doses of ICS (Trial 684 NCT00603746). The trials in Figure 3 were dose-ranging trials of ARNUITY ELLIPTA not designed to provide comparative effectiveness data and should not be interpreted as evidence of superiority/inferiority to fluticasone propionate. A dose-related increase in trough FEV1 at Week 8 was seen for doses from 25 to 200 mcg with no consistent additional benefit for doses above 200 mcg as seen in Figure 3. To evaluate dosing frequency, a separate trial compared fluticasone furoate 200 mcg once daily, fluticasone furoate 100 mcg twice daily, fluticasone propionate 100 mcg twice daily, and fluticasone propionate 200 mcg once daily. The results supported the selection of the once-daily dosing frequency.

Figure 3. Dose-Ranging Trials

FF = Fluticasone furoate, FP = Fluticasone propionate, OD = Once daily, BD = Twice daily.

14.2 Confirmatory Trials

Adult and Pediatric Subjects Aged 12 Years and Older

The clinical development program for ARNUITY ELLIPTA included 4 confirmatory trials in adult and pediatric subjects with asthma aged 12 years and older. The trials were designed to evaluate the safety and efficacy of ARNUITY ELLIPTA given once daily in the evening on lung function in subjects who were not controlled on their current treatments of ICS, or combination therapy consisting of an ICS plus a LABA. Study treatments were delivered as inhalation powders. The primary endpoint in all trials was change from baseline in evening trough FEV1 measured approximately 24 hours after the final dose of study medication. Trough FEV1 (assessed at approximately 24 hours after the previous dose) was also assessed at clinic visits throughout the trials. Trials 2 and 4 had a co-primary endpoint of change from baseline in weighted mean serial FEV1 measured after the final dose of study medication at 5, 15, and 30 minutes and 1, 2, 3, 4, 5, 12, 16, 20, 23, and 24 hours post-dose.

Clinical Trials with ARNUITY ELLIPTA 100 mcg: Trial 1 (NCT01159912) was a 24-week trial that evaluated the efficacy of ARNUITY ELLIPTA 100 mcg compared with placebo on lung function in subjects with asthma. Inhaled fluticasone propionate 250 mcg twice daily was included as an active control. Of the 343 subjects, 59% were female and 79% were Caucasian. The mean age was 41 years. The trial included a 4-week run-in period during which the subjects were symptomatic while taking their usual low- to mid-dose ICS therapy (i.e., fluticasone propionate 100 to 500 mcg daily or equivalent). Mean baseline percent predicted FEV1 was approximately 73% overall and was similar across the 3 treatment groups. Thirty-five percent of subjects on placebo and 19% of subjects on ARNUITY ELLIPTA 100 mcg failed to complete the 24-week trial.

The change in trough FEV1 from baseline to Week 24, or the last available on-treatment visit prior to Week 24, was assessed to evaluate the efficacy of ARNUITY ELLIPTA 100 mcg. The mean change from baseline in trough FEV1 was greater among subjects receiving ARNUITY ELLIPTA 100 mcg than among those receiving placebo (mean treatment difference from placebo 146 mL; 95% CI: 36, 257) as shown in Table 3.

Table 3. Change from Baseline in Trough FEV1 (mL) at Week 24 – Trial 1
Trough FEV1 (Week 24) | Placebo; (n = 113) | ARNUITY ELLIPTA; 100 mcg; (n = 111) | Fluticasone Propionate; 250 mcg; Twice Daily; (n = 107)
Least squares mean | 2,372 | 2,519 | 2,517
Least squares mean change (SE) | 15 (39.4) | 161 (39.8) | 159 (40.6)
Column vs. placebo
Difference | — | 146 | 145
95% CI | — | 36, 257 | 33, 257
P value | — | 0.009 | 0.011
FEV1 = forced expiratory volume in 1 second, SE = standard error.

Trial 2 (NCT01165138) was a 12-week trial that evaluated the efficacy of ARNUITY ELLIPTA 100 mcg on lung function in subjects with asthma compared with placebo. The combination of fluticasone furoate 100 mcg and vilanterol 25 mcg was also included as a treatment arm. Of the 609 subjects, 58% were female and 84% were Caucasian. The mean age was 40 years. The trial included a 4-week run-in period during which the subjects were symptomatic while taking their usual low- to mid-dose ICS (fluticasone propionate 200 to 500 mcg/day or equivalent). If LABA were used prior to screening, their use was discontinued during the run-in. Mean baseline percent predicted FEV1 was approximately 70% in both treatment groups. Twenty-six percent of subjects on placebo and 10% of subjects on ARNUITY ELLIPTA 100 mcg failed to complete the 12-week trial.

The co-primary efficacy endpoints in Trial 2 were change from baseline in trough FEV1 at Week 12 and weighted mean FEV1 (0-24 hours) at the end of the 12-week treatment period. Trough FEV1 was assessed at clinic visits throughout the trial. Weighted mean FEV1 (0-24 hours) was recorded at baseline and after the final study dose with serial measurements taken at frequent intervals (at 5, 15, and 30 minutes and 1, 2, 3, 4, 5, 12, 16, 20, 23, and 24 hours post-dose) in a subset of subjects (n = 201).

ARNUITY ELLIPTA 100 mcg once daily had greater mean changes from baseline in trough FEV1 than placebo throughout the trial. At Week 12 or the last available on-treatment visit prior to Week 12, the mean change from baseline in trough FEV1 was greater among subjects receiving ARNUITY ELLIPTA 100 mcg once daily than among those receiving placebo (mean treatment difference 136 mL; 95% CI: 51, 222).

Lung function improvements were sustained over the 24-hour period following the final dose of ARNUITY ELLIPTA 100 mcg (Figure 4). Compared with placebo, at Week 12 the change from baseline in weighted mean FEV1 was significantly greater for ARNUITY ELLIPTA 100 mcg (mean treatment difference 186 mL; 95% CI: 62, 310).

Figure 4. Mean Change from Baseline in Individual Serial FEV1 (mL) Assessments after 12 Weeks of Treatment – Trial 2

Subjects in both Trials 1 and 2 receiving ARNUITY ELLIPTA 100 mcg once daily had a greater improvement from baseline in percentage of 24-hour periods without need of beta2-agonist rescue medication use than subjects receiving placebo.

Clinical Trial with ARNUITY ELLIPTA 200 mcg: Trial 3 (NCT01431950) was a 24-week trial that evaluated the relative efficacy of ARNUITY ELLIPTA 100 mcg and ARNUITY ELLIPTA 200 mcg on lung function in subjects with asthma. Of the 219 subjects, 68% were female and 87% were Caucasian. The mean age was 46 years. The trial included a 4-week run-in period during which the subjects were symptomatic while taking their usual mid- to high-dose ICS therapy (i.e., fluticasone propionate greater than 250 to 1,000 mcg/day or equivalent). If LABA were used prior to screening, their use was discontinued during the run-in. Mean baseline percent predicted FEV1 was approximately 68% overall and similar in the 2 treatment groups. Sixteen percent of subjects on ARNUITY ELLIPTA 100 mcg and 13% of subjects on ARNUITY ELLIPTA 200 mcg failed to complete the 24-week trial.

The primary efficacy endpoint was mean change from baseline in trough FEV1 at Week 24. There were trends toward greater mean changes from baseline in the group receiving ARNUITY ELLIPTA 200 mcg than the group receiving ARNUITY ELLIPTA 100 mcg throughout the trial (Figure 5). At Week 24 or the last available on-treatment visit prior to Week 24, the mean change from baseline in trough FEV1 was 208 mL for ARNUITY ELLIPTA 100 mcg, as compared with 284 mL for ARNUITY ELLIPTA 200 mcg (difference of 77 mL; 95% CI: -39, 192) as seen in Figure 5.

Figure 5. Mean Change from Baseline in Trough FEV1 (mL) over Time – Trial 3

Trial 4 (NCT01134042) was a 24-week trial that evaluated the efficacy of ARNUITY ELLIPTA 200 mcg once daily and fluticasone propionate 500 mcg twice daily on lung function in subjects with asthma. The combination of fluticasone furoate 200 mcg and vilanterol 25 mcg was also included as a treatment arm (data not shown). Of the 586 subjects, 59% were female and 84% were Caucasian. The mean age was 46 years. The trial included a 4-week run-in period during which the subjects were symptomatic while taking their usual mid- to high-dose ICS (fluticasone propionate 500 to 1,000 mcg/day or equivalent). If LABA were used prior to screening, their use was discontinued during the run-in. Mean baseline percent predicted FEV1 was approximately 67% in both treatment groups.

Both ARNUITY ELLIPTA 200 mcg once daily and fluticasone propionate 500 mcg twice daily produced improvement from baseline in lung function. At Week 24 the mean change from baseline in trough FEV1 was 201 mL for ARNUITY ELLIPTA 200 mcg once daily and 183 mL for fluticasone propionate 500 mcg twice daily (treatment difference of 18 mL, 95% CI: -66, 102).

Lung function improvements were sustained over the 24-hour period following the final dose of ARNUITY ELLIPTA 200 mcg (Figure 6). At Week 24, the change from baseline in weighted mean FEV1 was 328 mL for ARNUITY ELLIPTA 200 mcg once daily and 258 mL for fluticasone propionate 500 twice daily (difference of 70 mL; 95% CI: -67, 208).

Figure 6. Mean Change from Baseline in Individual Serial FEV1 (mL) Assessments after 24 Weeks of Treatment – Trial 4

Pediatric Subjects Aged 5 to 11 Years

A 12-week trial (NCT01563029) evaluated the efficacy of fluticasone furoate (25, 50, or 100 mcg) administered once daily in the evening compared with placebo in 593 pediatric subjects with asthma aged 5 to 11 years. Inhaled fluticasone propionate 100 mcg twice daily was included as an active control. At trial entry subjects were symptomatic, had at least a 6-month history of asthma, and had been receiving stable asthma therapy for at least 4 weeks prior to screening. Subjects had to have a pre-bronchodilator PEF of ≥60% to ≤90% of their best post-bronchodilator value and, in subjects able to perform the maneuver, demonstrate a ≥12% reversibility of FEV1 within approximately 10 to 40 minutes following 2 to 4 inhalations of albuterol inhalation aerosol. The primary endpoint of this trial was the mean change from baseline in daily pre-dose AM PEF from the patient electronic daily diary averaged over the 12-week treatment period. A secondary endpoint was the change from baseline in the percentage of rescue-free 24-hour periods during the 12-week treatment period. Of the 593 subjects, the mean age was 8 years, 62% were male, and 42% were Caucasian. Lung function improvements based on the primary endpoint of mean change from baseline in AM PEF are presented in Table 4.

Table 4. Least Squares Mean Change from Baseline in Pre-Dose AM PEF over the 12-Week Treatment Period (Intent-to-Treat Population)
Primary Endpoint | Placebo; (n = 119) | Fluticasone Furoate; 25 mcg; (n = 118) | Fluticasone Furoate; 50 mcg; (n = 120) | Fluticasone Furoate; 100 mcg; (n = 118) | Fluticasone Propionate; 100 mcg; (n = 118)
AM PEF (L/min)a | n = 119 | n = 117 | n = 118 | n = 118 | n = 117
LS mean change (SE) | 3.3 (2.63) | 21.9 (2.66) | 22.8 (2.65) | 15.8 (2.64) | 17.3 (2.64)
Difference vs placebo |  | 18.6 | 19.5 | 12.5 | 14.0
(95% CI) |  | (11.3, 26.0) | (12.1, 26.9) | (5.1, 19.8) | (6.7, 21.4)
AM PEF = Morning Peak Expiratory Flow, LS = Least squares, SE = standard error.
a Average over Weeks 1 to 12.

Pediatric subjects receiving ARNUITY ELLIPTA 50 mcg had a greater improvement from baseline in percentage of 24-hour periods without need of beta2-agonist rescue medication use than subjects receiving placebo.

Given the demonstration of efficacy of ARNUITY ELLIPTA 100 mcg and ARNUITY ELLIPTA 200 mcg in the adult and pediatric population aged 12 years and older, the results support the efficacy of ARNUITY ELLIPTA 50 mcg once daily in pediatric subjects with asthma aged 5 to 11 years.

16 HOW SUPPLIED/STORAGE AND HANDLING

ARNUITY ELLIPTA 50 mcg is supplied as a disposable light grey and orange plastic inhaler containing a foil strip with 30 blisters (NDC 0173-0888-10).

ARNUITY ELLIPTA 100 mcg is supplied as a disposable light grey and orange plastic inhaler containing a foil strip with 30 blisters (NDC 0173-0874-10) or 14 blisters (institutional pack) (NDC 0173-0874-14).

ARNUITY ELLIPTA 200 mcg is supplied as a disposable light grey and orange plastic inhaler containing a foil strip with 30 blisters (NDC 0173-0876-10) or 14 blisters (institutional pack) (NDC 0173-0876-14).

The inhaler is packaged in a moisture-protective foil tray with a desiccant and a peelable lid.

Store at room temperature between 68°F and 77°F (20°C and 25°C); excursions permitted from 59°F to 86°F (15°C to 30°C) [See USP Controlled Room Temperature]. Store in a dry place away from direct heat or sunlight. Keep out of reach of children.

ARNUITY ELLIPTA should be stored inside the unopened moisture-protective foil tray and only removed from the tray immediately before initial use. Discard ARNUITY ELLIPTA 6 weeks after opening the foil tray or when the counter reads “0” (after all blisters have been used), whichever comes first. The inhaler is not reusable. Do not attempt to take the inhaler apart.

17 PATIENT COUNSELING INFORMATION

Advise the patient to read the FDA-approved patient labeling (Patient Information and Instructions for Use).

Not for Acute Symptoms

Inform patients that ARNUITY ELLIPTA is not meant to relieve acute symptoms of asthma and extra doses should not be used for that purpose. Advise patients to treat acute symptoms with an inhaled, short-acting beta2-agonist such as albuterol. Provide patients with such medication and instruct them in how it should be used.

Instruct patients to seek medical attention immediately if they experience any of the following:

- Decreasing effectiveness of inhaled, short-acting beta2-agonists
- Need for more inhalations than usual of inhaled, short-acting beta2-agonists
- Significant decrease in lung function as outlined by the physician

Advise patients not to increase the dose or frequency of ARNUITY ELLIPTA. The daily dosage of ARNUITY ELLIPTA should not exceed 1 inhalation. If they miss a dose, instruct patients to take it as soon as they remember, not to exceed 1 inhalation per day. Advise patients to take their next dose at the same time they normally do and to not take 2 doses at 1 time.

Tell patients they should not stop therapy with ARNUITY ELLIPTA without physician/provider guidance since symptoms may recur after discontinuation. [See Warnings and Precautions (5.2).]

Oropharyngeal Candidiasis

Inform patients that localized infections with Candida albicans occurred in the mouth and pharynx in some patients. If oropharyngeal candidiasis develops, treat it with appropriate local or systemic (i.e., oral) antifungal therapy while still continuing therapy with ARNUITY ELLIPTA, but at times therapy with ARNUITY ELLIPTA may need to be temporarily interrupted under close medical supervision. Advise patients to rinse the mouth with water without swallowing after inhalation to help reduce the risk of thrush. [See Warnings and Precautions (5.1).]

Immunosuppression and Risk of Infections

Warn patients who are on immunosuppressant doses of corticosteroids to avoid exposure to chickenpox or measles and, if exposed, to consult their physicians without delay. Inform patients of potential worsening of existing tuberculosis, fungal, bacterial, viral, or parasitic infections or ocular herpes simplex. [See Warnings and Precautions (5.3).]

Hypercorticism and Adrenal Suppression

Advise patients that ARNUITY ELLIPTA may cause systemic corticosteroid effects of hypercorticism and adrenal suppression. Additionally, inform patients that deaths due to adrenal insufficiency have occurred during and after transfer from systemic corticosteroids. Patients should taper slowly from systemic corticosteroids if transferring to ARNUITY ELLIPTA. [See Warnings and Precautions (5.5).]

Hypersensitivity Reactions, including Anaphylaxis

Advise patients that hypersensitivity reactions (e.g., anaphylaxis, angioedema, urticaria, flushing, allergic dermatitis, bronchospasm) may occur after administration of ARNUITY ELLIPTA. Instruct patients to discontinue ARNUITY ELLIPTA if such reactions occur. There have been reports of anaphylactic reactions in patients with severe milk protein allergy after inhalation of other powder medications containing lactose; therefore, patients with severe milk protein allergy should not use ARNUITY ELLIPTA. [See Warnings and Precautions (5.8).]

Reduction in Bone Mineral Density

Advise patients who are at an increased risk for decreased BMD that the use of corticosteroids may pose an additional risk. [See Warnings and Precautions (5.9)]

Reduced Growth Velocity

Inform patients that orally inhaled corticosteroids, including ARNUITY ELLIPTA, may cause a reduction in growth velocity when administered to pediatric patients. Physicians should closely follow the growth of pediatric patients taking corticosteroids by any route. [See Warnings and Precautions (5.10).]

Glaucoma and Cataracts

Advise patients that long-term use of ICS may increase the risk of some eye problems (cataracts or glaucoma); consider regular eye examinations. [See Warnings and Precautions (5.11).]

Use Daily for Best Effect

Advise patients to use ARNUITY ELLIPTA at regular intervals, since its effectiveness depends on regular use. Maximum benefit may not be achieved for 1 week or longer after starting treatment. If symptoms do not improve after 2 weeks of therapy or if the condition worsens, instruct patients to contact their physicians.

Trademarks are owned by or licensed to the GSK group of companies.

GlaxoSmithKline

Durham, NC 27701

©2023 GSK group of companies or its licensor.

ARN:11PI

Patient Information

ARNUITY ELLIPTA (ar-NEW-i-te e-LIP-ta)

(fluticasone furoate inhalation powder)

for oral inhalation use

What is ARNUITY ELLIPTA?

- ARNUITY ELLIPTA is an inhaled corticosteroid (ICS) medicine (fluticasone furoate).
  - ICS medicines such as fluticasone furoate help to decrease inflammation in the lungs. Inflammation in the lungs can lead to breathing problems.
- ARNUITY ELLIPTA is not used to relieve sudden breathing problems and will not replace a rescue inhaler.
- ARNUITY ELLIPTA is a prescription medicine used to prevent and control symptoms of asthma for better breathing.

It is not known if ARNUITY ELLIPTA is safe and effective in children younger than 5 years of age.

Do not use ARNUITY ELLIPTA:

- to treat sudden symptoms of asthma.
- if you have a severe allergy to milk proteins. Ask your healthcare provider if you are not sure.
- if you are allergic to fluticasone furoate or any of the ingredients in ARNUITY ELLIPTA. See the end of this Patient Information for a complete list of ingredients in ARNUITY ELLIPTA.

Before using ARNUITY ELLIPTA, tell your healthcare provider about all of your medical conditions, including if you:

- have liver problems.
- have weak bones (osteoporosis).
- have an immune system problem.
- have eye problems such as glaucoma, increased pressure in your eye, cataracts, or other changes in vision.
- are allergic to milk proteins.
- have any type of viral, bacterial, fungal, or parasitic infection.
- are exposed to chickenpox or measles.
- are pregnant or plan to become pregnant. It is not known if ARNUITY ELLIPTA may harm your unborn baby.
- are breastfeeding or plan to breastfeed. It is not known if the medicine in ARNUITY ELLIPTA passes into your breast milk and if it can harm your baby.

Tell your healthcare provider about all the medicines you take, including prescription and over-the-counter medicines, vitamins, and herbal supplements. ARNUITY ELLIPTA and certain other medicines may interact with each other. This may cause serious side effects. Especially, tell your healthcare provider if you take antifungal, anti-HIV, or any other corticosteroid medicines.

Know the medicines you take. Keep a list of them to show your healthcare provider and pharmacist when you get a new medicine.

How should I use ARNUITY ELLIPTA?

Read the step-by-step instructions for using ARNUITY ELLIPTA at the end of this Patient Information.

- Do not use ARNUITY ELLIPTA unless your healthcare provider has taught you how to use the inhaler and you understand how to use it correctly.
- ARNUITY ELLIPTA comes in 3 different strengths. Your healthcare provider prescribed the strength that is best for you.
- Use ARNUITY ELLIPTA exactly as your healthcare provider tells you to use it. Do not use ARNUITY ELLIPTA more often than prescribed.
- Children and adolescents may need help to use ARNUITY ELLIPTA.
- Use 1 inhalation of ARNUITY ELLIPTA 1 time each day. Use ARNUITY ELLIPTA at the same time each day.
- If you miss a dose of ARNUITY ELLIPTA, take it as soon as you remember. Do not take more than 1 inhalation per day. Take your next dose at your usual time. Do not take 2 doses at 1 time.
- Do not stop using ARNUITY ELLIPTA unless told to do so by your healthcare provider because your symptoms might get worse. Your healthcare provider will change your medicines as needed.
- ARNUITY ELLIPTA does not relieve sudden symptoms of asthma and you should not take extra doses of ARNUITY ELLIPTA to relieve these sudden symptoms. Always have a rescue inhaler with you to treat sudden symptoms. If you do not have a rescue inhaler, call your healthcare provider to have one prescribed for you.
- Call your healthcare provider or get medical care right away if:
  - your breathing problems get worse.
  - you need to use your rescue inhaler more often than usual.
  - your rescue inhaler does not work as well to relieve your symptoms.
  - your peak flow meter results decrease. Your healthcare provider will tell you the numbers that are right for you.

What are the possible side effects of ARNUITY ELLIPTA?

ARNUITY ELLIPTA can cause serious side effects, including:

- fungal infection in your mouth or throat (thrush). Rinse your mouth with water without swallowing after using ARNUITY ELLIPTA to help reduce your chance of getting thrush.
- weakened immune system and increased chance of getting infections (immunosuppression).
- reduced adrenal function (adrenal insufficiency). Adrenal insufficiency is a condition where the adrenal glands do not make enough steroid hormones. This can happen when you stop taking oral corticosteroid medicines (such as prednisone) and start taking a medicine containing an ICS (such as ARNUITY ELLIPTA). During this transition period, when your body is under stress from fever, trauma (such as a car accident), infection, surgery, or worse asthma symptoms, adrenal insufficiency can get worse and may cause death.
  Symptoms of adrenal insufficiency include:

- feeling tired

- nausea and vomiting

- lack of energy

- low blood pressure (hypotension)

- weakness

- sudden breathing problems immediately after inhaling your medicine. If you have sudden breathing problems immediately after inhaling your medicine, stop using ARNUITY ELLIPTA and call your healthcare provider right away.
- serious allergic reactions. Call your healthcare provider or get emergency medical care if you get any of the following symptoms of a serious allergic reaction:

- rash

- swelling of your face, mouth, and tongue

- hives

- breathing problems

- bone thinning or weakness (osteoporosis).
- slow growth in children and adolescents. A child’s or adolescent’s growth should be checked often.
- eye problems including glaucoma, increased pressure in your eye, cataracts, or other changes in vision. You should have regular eye exams while using ARNUITY ELLIPTA.

Common side effects of ARNUITY ELLIPTA include:

- runny nose and sore throat

- breathing problems (bronchitis)

- headache

- flu

These are not all the possible side effects of ARNUITY ELLIPTA.

Call your doctor for medical advice about side effects. You may report side effects to FDA at 1-800-FDA-1088.

How should I store ARNUITY ELLIPTA?

- Store ARNUITY ELLIPTA at room temperature between 68°F and 77°F (20°C and 25°C). Keep in a dry place away from heat and sunlight.
- Store ARNUITY ELLIPTA in the unopened tray and only open when ready for use.
- Safely throw away ARNUITY ELLIPTA in the trash 6 weeks after you open the tray or when the counter reads “0”, whichever comes first. Write the date you open the tray on the label on the inhaler.

Keep ARNUITY ELLIPTA and all medicines out of the reach of children.

General information about the safe and effective use of ARNUITY ELLIPTA.

Medicines are sometimes prescribed for purposes other than those listed in a Patient Information leaflet. Do not use ARNUITY ELLIPTA for a condition for which it was not prescribed. Do not give ARNUITY ELLIPTA to other people, even if they have the same symptoms that you have. It may harm them.

You can ask your healthcare provider or pharmacist for information about ARNUITY ELLIPTA that is written for health professionals.

What are the ingredients in ARNUITY ELLIPTA?

Active ingredients: fluticasone furoate

Inactive ingredients: lactose monohydrate (contains milk proteins)

For more information about ARNUITY ELLIPTA, call 1-888-825-5249.

Trademarks are owned by or licensed to the GSK group of companies.

GlaxoSmithKline, Durham, NC 27701

©2023 GSK group of companies or its licensor.

ARN:5PIL

This Patient Information has been approved by the U.S. Food and Drug Administration Revised: March 2023

INSTRUCTIONS FOR USE

ARNUITY ELLIPTA (ar-NEW-i-te e-LIP-ta)

(fluticasone furoate inhalation powder)

for oral inhalation use

Read this before you start:

- If you open and close the cover without inhaling the medicine, you will lose the dose.
- The lost dose will be securely held inside the inhaler, but it will no longer be available to be inhaled.
- It is not possible to accidentally take a double dose or an extra dose in 1 inhalation.

Your ARNUITY ELLIPTA inhaler

How to use your inhaler

- ARNUITY ELLIPTA comes in a tray.
- Peel back the lid to open the tray. See Figure A.
- The tray contains a desiccant to reduce moisture. Do not eat or inhale. Throw it away in the household trash out of reach of children and pets. See Figure B.

Figure A

Figure B

Important Notes:

- Your inhaler contains 30 doses (14 doses if you have a 100-mcg or 200-mcg strength sample or institutional pack).
- Each time you fully open the cover of the inhaler (you will hear a clicking sound), a dose is ready to be inhaled. This is shown by a decrease in the number on the counter.
- If you open and close the cover without inhaling the medicine, you will lose the dose. The lost dose will be held in the inhaler, but it will no longer be available to be inhaled. It is not possible to accidentally take a double dose or an extra dose in 1 inhalation.
- Do not open the cover of the inhaler until you are ready to use it. To avoid wasting doses after the inhaler is ready, do not close the cover until after you have inhaled the medicine.
- Write the “Tray opened” and “Discard” dates on the inhaler label. The “Discard” date is 6 weeks from the date you open the tray.

Check the counter. See Figure C.

Figure C

- Before the inhaler is used for the first time, the counter should show the number 30 (14 if you have a 100-mcg or 200-mcg strength sample or institutional pack). This is the number of doses in the inhaler.
- Each time you open the cover, you prepare 1 dose of medicine.
- The counter counts down by 1 each time you open the cover.

Prepare your dose:

Wait to open the cover until you are ready to take your dose.

Figure D

Step 1. Open the cover of the inhaler. See Figure D.

- Slide the cover down to expose the mouthpiece. You should hear a “click.” The counter will count down by 1 number. You do not need to shake this kind of inhaler. Your inhaler is now ready to use.
- If the counter does not count down as you hear the click, the inhaler will not deliver the medicine. Call your healthcare provider or pharmacist if this happens.

Figure E

Step 2. Breathe out. See Figure E.

- While holding the inhaler away from your mouth, breathe out (exhale) fully. Do not breathe out into the mouthpiece.

Figure F

Step 3. Inhale your medicine. See Figure F.

- Put the mouthpiece between your lips, and close your lips firmly around it. Your lips should fit over the curved shape of the mouthpiece.
- Take 1 long, steady, deep breath in through your mouth. Do not breathe in through your nose.

Figure G

- Do not block the air vent with your fingers. See Figure G.

Figure H

- Remove the inhaler from your mouth and hold your breath for about 3 to 4 seconds (or as long as comfortable for you). See Figure H.

Figure I

Step 4. Breathe out slowly and gently. See Figure I.

- You may not taste or feel the medicine, even when you are using the inhaler correctly.
- Do not take another dose from the inhaler even if you do not feel or taste the medicine.

Figure J

Step 5. Close the inhaler. See Figure J.

- You can clean the mouthpiece if needed, using a dry tissue, before you close the cover. Routine cleaning is not required.
- Slide the cover up and over the mouthpiece as far as it will go.

Figure K

Step 6. Rinse your mouth. See Figure K.

- Rinse your mouth with water after you have used the inhaler and spit the water out. Do not swallow the water.

Important Note: When should you get a refill?

Figure L

- When you have fewer than 10 doses remaining in your inhaler, the left half of the counter shows red as a reminder to get a refill. See Figure L.
- After you have inhaled the last dose, the counter will show “0” and will be empty.
- Throw the empty inhaler away in your household trash out of reach of children and pets.

For more information about ARNUITY ELLIPTA or how to use your inhaler, call 1-888-825-5249.

Trademarks are owned by or licensed to the GSK group of companies.

GlaxoSmithKline, Durham, NC 27701

©2023 GSK group of companies or its licensor.

ARN:2IFU

This Instructions for Use has been approved by the U.S. Food and Drug Administration Revised: March 2023

PACKAGE LABEL

PRINCIPAL DISPLAY PANEL

NDC 0173-0888-10

ARNUITY ELLIPTA\

(fluticasone furoate inhalation powder)

50 mcg

Rx Only

FOR ORAL INHALATION ONLY

Each blister contains 50 mcg of fluticasone furoate and lactose monohydrate.

1 ELLIPTA Inhaler containing 1 Foil Strip of 30 Blisters

GSK

Made in Singapore

©2023 GSK group of companies or its licensor.

62000000087776 Rev. 4/23

PACKAGE LABEL

PRINCIPAL DISPLAY PANEL

NDC 0173-0874-10

ARNUITY ELLIPTA

(fluticasone furoate inhalation powder)

100 mcg

Rx Only

FOR ORAL INHALATION ONLY

Each blister contains 100 mcg of fluticasone furoate and lactose monohydrate.

1 ELLIPTA Inhaler containing 1 Foil Strip of 30 Blisters

GSK

Made in Singapore

©2023 the GSK group of companies or its licensor.

62000000087842 Rev. 4/23

PACKAGE LABEL

PRINCIPAL DISPLAY PANEL

NDC 0173-0876-10

ARNUITYELLIPTA

(fluticasone furoate inhalation powder)

200 mcg

Rx Only

FOR ORAL INHALATION ONLY

Each blister contains 200 mcg of fluticasone furoate and lactose monohydrate.

1 ELLIPTA Inhaler containing 1 Foil Strip of 30 Blisters

GSK

Made in Singapore

©2023 the GSK group of companies

62000000087779 Rev. 4/23